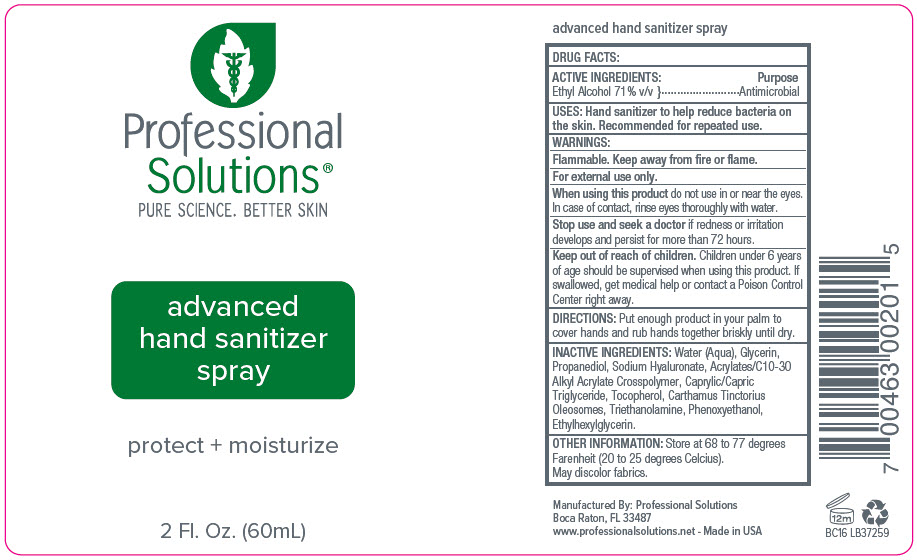 DRUG LABEL: Professional solutions - Advanced Hand Sanitizer
NDC: 66163-1600 | Form: SPRAY
Manufacturer: Cosmetic Solutions LLC
Category: otc | Type: HUMAN OTC DRUG LABEL
Date: 20200918

ACTIVE INGREDIENTS: Alcohol 71 mL/100 mL
INACTIVE INGREDIENTS: Water; Glycerin; Propanediol; Hyaluronate Sodium; CARBOMER INTERPOLYMER TYPE A (ALLYL SUCROSE CROSSLINKED); Medium-Chain Triglycerides; Tocopherol; CARTHAMUS TINCTORIUS SEED OLEOSOMES; Trolamine; Phenoxyethanol; Ethylhexylglycerin

Professional Solutions® - Advanced Hand Sanitizer Spray

DRUG FACTS

ACTIVE INGREDIENTS

Ethyl Alcohol 71% v/v

Purpose

Antimicrobial

USES

Hand sanitizer to help reduce bacteria on the skin. Recommended for repeated use.

WARNINGS

Flammable. Keep away from fire or flame.

For external use only.

When using this product do not use in or near the eyes. In case of contact, rinse eyes thoroughly with water.

Stop use and seek a doctor if redness or irritation develops and persist for more than 72 hours.

Keep out of reach of children. Children under 6 years of age should be supervised when using this product. If swallowed, get medical help or contact a Poison Control Center right away.

DIRECTIONS

Put enough product in your palm to cover hands and rub hands together briskly until dry.

INACTIVE INGREDIENTS

Water (Aqua), Glycerin, Propanediol, Sodium Hyaluronate, Acrylates/C10-30 Alkyl Acrylate Crosspolymer, Caprylic/Capric Triglyceride, Tocopherol, Carthamus Tinctorius Oleosomes, Triethanolamine, Phenoxyethanol, Ethylhexylglycerin.

OTHER INFORMATION

Store at 68 to 77 degrees Farenheit (20 to 25 degrees Celcius).

May discolor fabrics.

Manufactured By: Professional Solutions
Boca Raton, FL 33487

PRINCIPAL DISPLAY PANEL - 60 mL Bottle Label

Professional
Solutions®
PURE SCIENCE. BETTER SKIN

advanced
hand sanitizer
spray

protect + moisturize

2 Fl. Oz. (60mL)